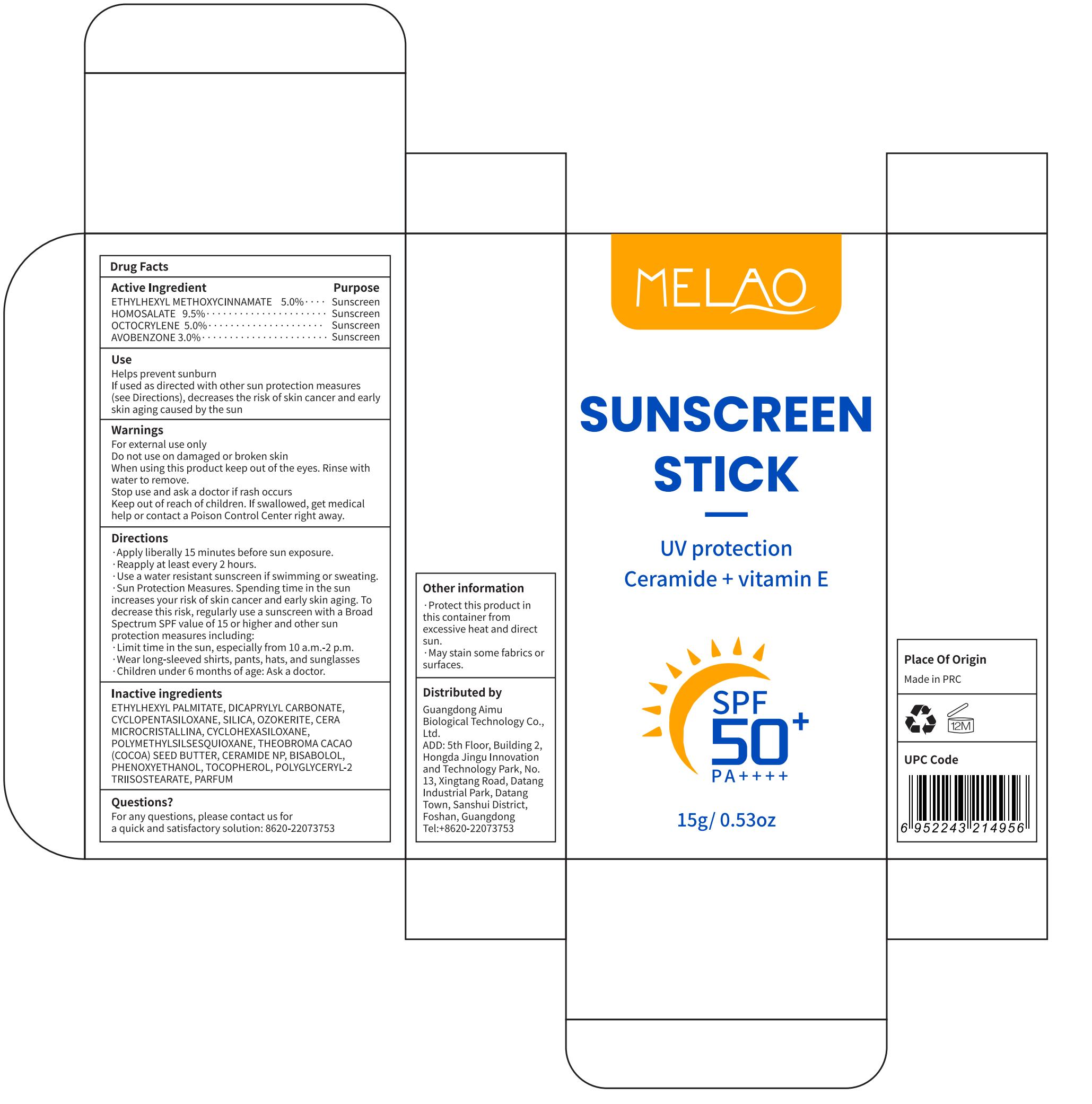 DRUG LABEL: MELAO Sunscreen Stick
NDC: 83566-564 | Form: STICK
Manufacturer: Guangdong Aimu Biological Technology Co., Ltd
Category: otc | Type: HUMAN OTC DRUG LABEL
Date: 20260226

ACTIVE INGREDIENTS: OCTOCRYLENE 5 g/100 g; AVOBENZONE 3 g/100 g; ETHYLHEXYL METHOXYCINNAMATE 5 g/100 g; HOMOSALATE 9.5 g/100 g
INACTIVE INGREDIENTS: BISABOLOL; DICAPRYLYL CARBONATE; ETHYLHEXYL PALMITATE; TOCOPHEROL; POLYMETHYLSILSESQUIOXANE (11 MICRONS); CYCLOHEXASILOXANE; PHENOXYETHANOL; MICROCRYSTALLINE WAX; CERAMIDE NP; CYCLOPENTASILOXANE; SILICA; THEOBROMA CACAO (COCOA) SEED BUTTER; POLYGLYCERYL-2 TRIISOSTEARATE; CERESIN

MELAO Sunscreen Stick

Active Ingredient

ETHYLHEXYL METHOXYCINNAMATE 5.0%
HOMOSALATE 9.5%
OCTOCRYLENE 5.0%
AVOBENZONE 3.0%

Purpose

Sunscreen

Use

Helps prevent sunburn
If used as directed with other sun protection measures (see Directions), decreases the risk of skin cancer and early skin aging caused by the sun

Warnings

For external use only.

Stop use and ask a doctor if

rash occurs

Do not use

on damaged or broken skin

When using this product

keep out of the eyes. Rinse with water to remove.

Keep out of reach of children.

If swallowed, get medical help or contact a Poison Control Center right away.

Directions

·Apply liberally 15 minutes before sun exposure.
·Reapply at least every 2 hours.
·Use a water resistant sunscreen if swimming or sweating.
·Sun Protection Measures. Spending time in the sun increases your risk of skin cancer and early skin aging. To decrease this risk, regularly use a sunscreen with a Broad Spectrum SPF value of 15 or higher and other sun protection measures including:
·Limit time in the sun, especially from 10 a.m.-2 p.m.
·Wear long-sleeved shirts, pants, hats, and sunglasses
·Children under 6 months of age: Ask a doctor.

Inactive ingredients

ETHYLHEXYL PALMITATE, DICAPRYLYL CARBONATE, CYCLOPENTASILOXANE, SILICA, OZOKERITE, CERA MICROCRISTALLINA, CYCLOHEXASILOXANE, POLYMETHYLSILSESQUIOXANE, THEOBROMA CACAO (COCOA) SEED BUTTER, CERAMIDE NP, BISABOLOL, PHENOXYETHANOL, TOCOPHEROL, POLYGLYCERYL-2 TRIISOSTEARATE, PARFUM

Other information

·Protect this product in this container from excessive heat and direct sun.

·May stain some fabrics or surfaces.

Questions or comments?

For any questions, please contact us for a quick and satisfactory solution: 8620-22073753